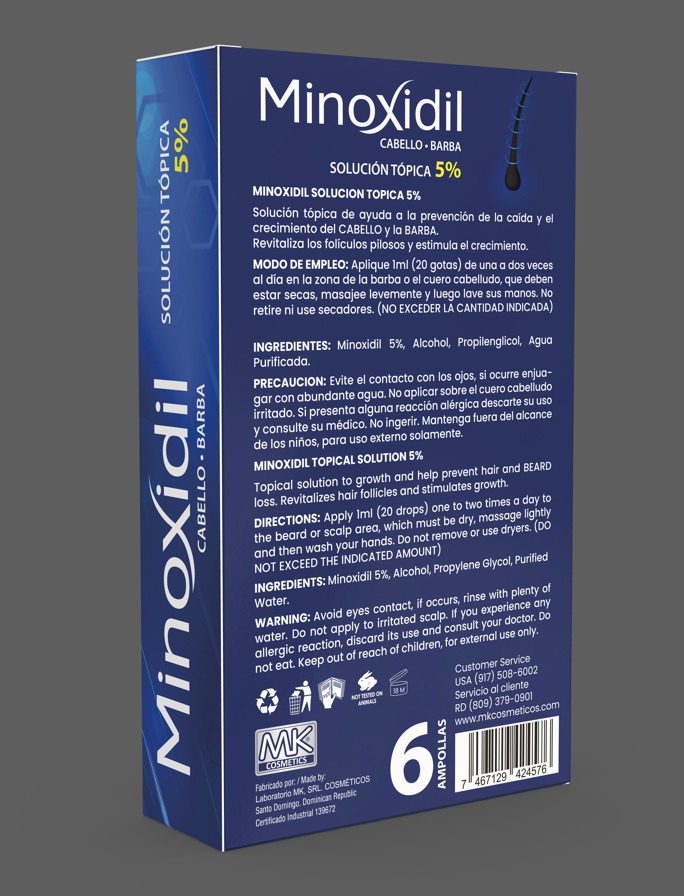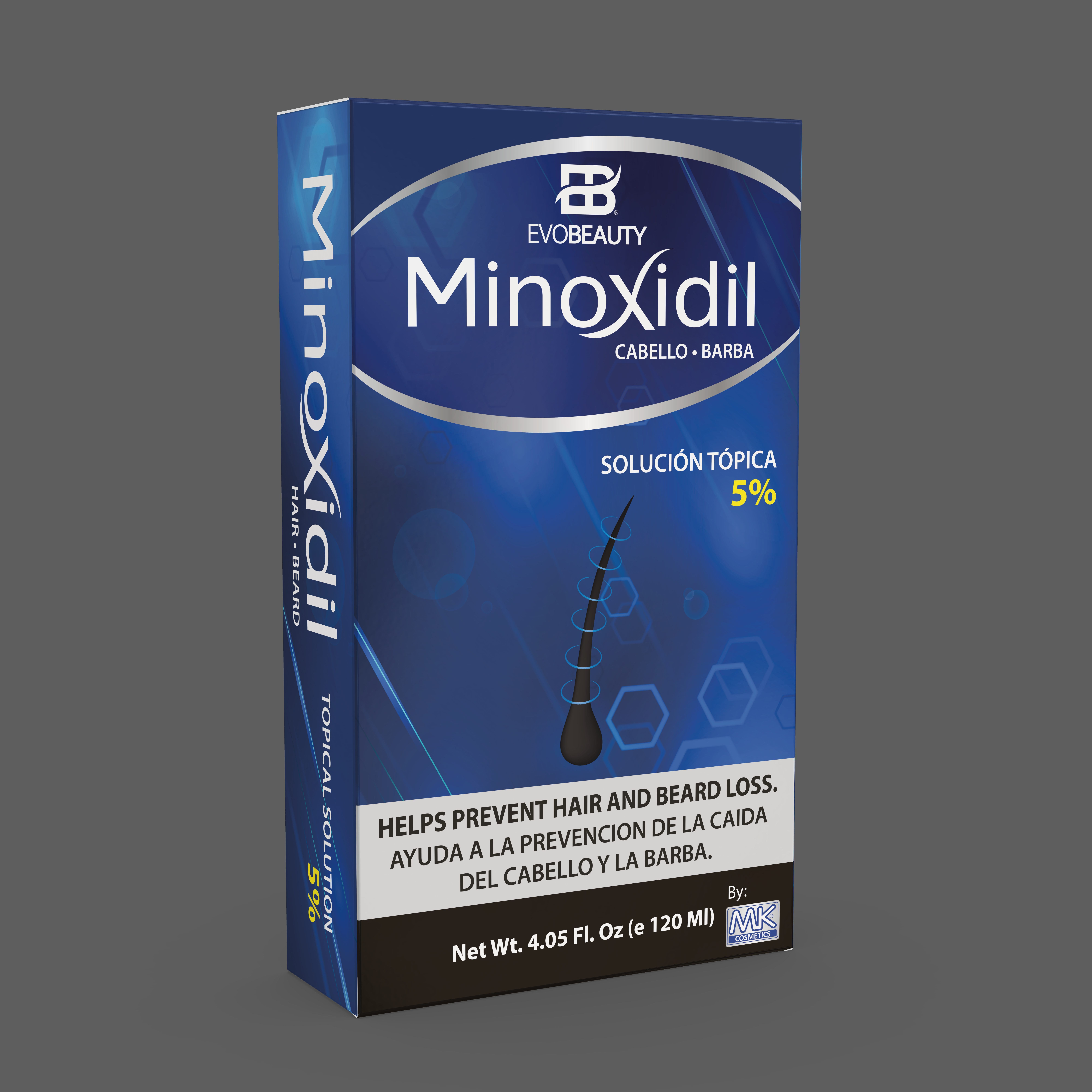 DRUG LABEL: hair growth solution
NDC: 87022-006 | Form: LIQUID
Manufacturer: LABORATORIO MK SRL
Category: otc | Type: HUMAN OTC DRUG LABEL
Date: 20250829

ACTIVE INGREDIENTS: MINOXIDIL 5 mg/20 mL
INACTIVE INGREDIENTS: WATER; ALCOHOL 50%; PROPYLENE GLYCOL 1,2-DISTEARATE

INDICATIONS AND USAGE

Apply 1ml (20 drops) one to two times a day to the beard or scalp area, which must be dry, massage lightly and then wash your hands. Do not remove or use dryers. (Do not exceed the indicated amount)

INACTIVE INGREDIENT

Alcohol, Propylen Glycol, Purified Water.

WARNINGS

Avoid eyes contact, if occurs, rinse with plenty of water. Do not apply to irritated scalp. If yoy experience any allergic reaction discard its use and consult your doctor. Do not eat.

DOSAGE AND ADMINISTRATION

Apply 1ml (20 drops) one to two times a day to the beard or scalp area.

Keep out of reach of children, for external use only.